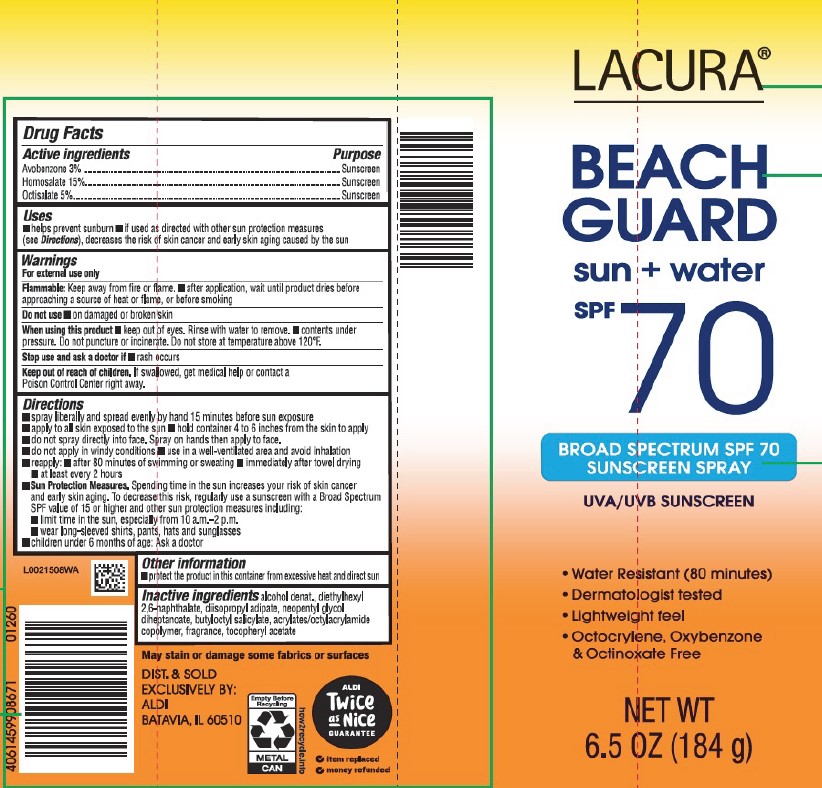 DRUG LABEL: Sunscreen SPF 70
NDC: 64024-938 | Form: SPRAY
Manufacturer: Aldi, Inc
Category: otc | Type: HUMAN OTC DRUG LABEL
Date: 20260129

ACTIVE INGREDIENTS: AVOBENZONE 30 mg/1 g; HOMOSALATE 150 mg/1 g; OCTISALATE 50 mg/1 g
INACTIVE INGREDIENTS: ALCOHOL; DIETHYLHEXYL 2,6-NAPHTHALATE; DIISOPROPYL ADIPATE; NEOPENTYL GLYCOL DIHEPTANOATE; BUTYLOCTYL SALICYLATE; ACRYLATE/ISOBUTYL METHACRYLATE/N-TERT-OCTYLACRYLAMIDE COPOLYMER (75000 MW); .ALPHA.-TOCOPHEROL ACETATE

Lacura D38.000/D38AA
Beach Guard Sunscreen Spray SPF 70

Active ingredients

Avobenzone 3%

Homosalate 15%

Octisalate 5%

Purpose

Sunscreen

Uses

- helps prevent sunburn
- if used as directed with other sun protection measures (see Directions), decreases the risk of skin cancer and early skin aging caused by the sun

Warnings

For external use only

Flammable

Keep away from fire or flame.

- after application, wait until product dries before approacing a souce of heat or flame, or before smoking

Do not use

- on damaged or broken skin

When using this product

- keep out of eyes. Rinse with water to remove.
- contents under pressure. Do not puncture or incinerate. Do not store at temperature above 120ºF.

Stop use and ask a doctor if

- rash occurs

Keep out of reach of children

If swallowed, get medical help or contact a Poison Conrol Center right away.

Directions

- spray liberally and spread evenly by hand 15 minutes before sun exposure
- apply to all skin exposed to the sun
- hold container 4 to 6 inches from the skin to apply
- do not spray directly into face. Spray on hands then apply to face.
- do not apply in windy conditions
- use in a well-ventilated area and avoid inhalation
- reapply:
- after 80 minutes of swimming or sweating
- immediately after towel drying
- at least every 2 hours
- Sun Protection Measures. Spending time in the sun increases your risk of skin cancer and early skin aging. To decrease this risk, regularly use a sunscreen with a Broad Spectrum SPF value of 15 or higher and other sun protection measures including:
- limit time in the sun, especially from 10 a.m.–2 p.m.
- wear long-sleeved shirts, pants, hats and sunglasses
- children under 6 months of age: Ask a doctor

Other information

- protect the product in the container from excessive heat and direct sun

Inactive ingredients

alcohol denat., diethylhexyl 2,6-naphthalate, diisopropyl adipate, neopentyl glycol diheptanoate, butyloctyl salicylate, acrylates/octylacrylamide copolymer, fragrance, tocopheryl acetate

Disclaimer

May stain or damage some fabrics of surfaces

Adverse reaction

DIST. & sold exclusively by:

ALDI

BATAVIA, IL 60510

ALDI TWICE as Nice Guarantee

- item replaced
- money refunded

how2recycle.info

Empty Before Recycling

METAL CAN

Principal display panel

LACURA®

BEACH GUARD

sun + water

SPF 70

BROAD SPECTRUM SPF 70

SUNSCREEN SPRAY

UVA/UVB SUNSCREEN

- Water-Resistant (80 minutes)
- Dermatologist tested
- Lightweight feel
- Octocrylene, Oxybenzone & Octinoxate Free

NET WT 6.5 OZ (184 g)